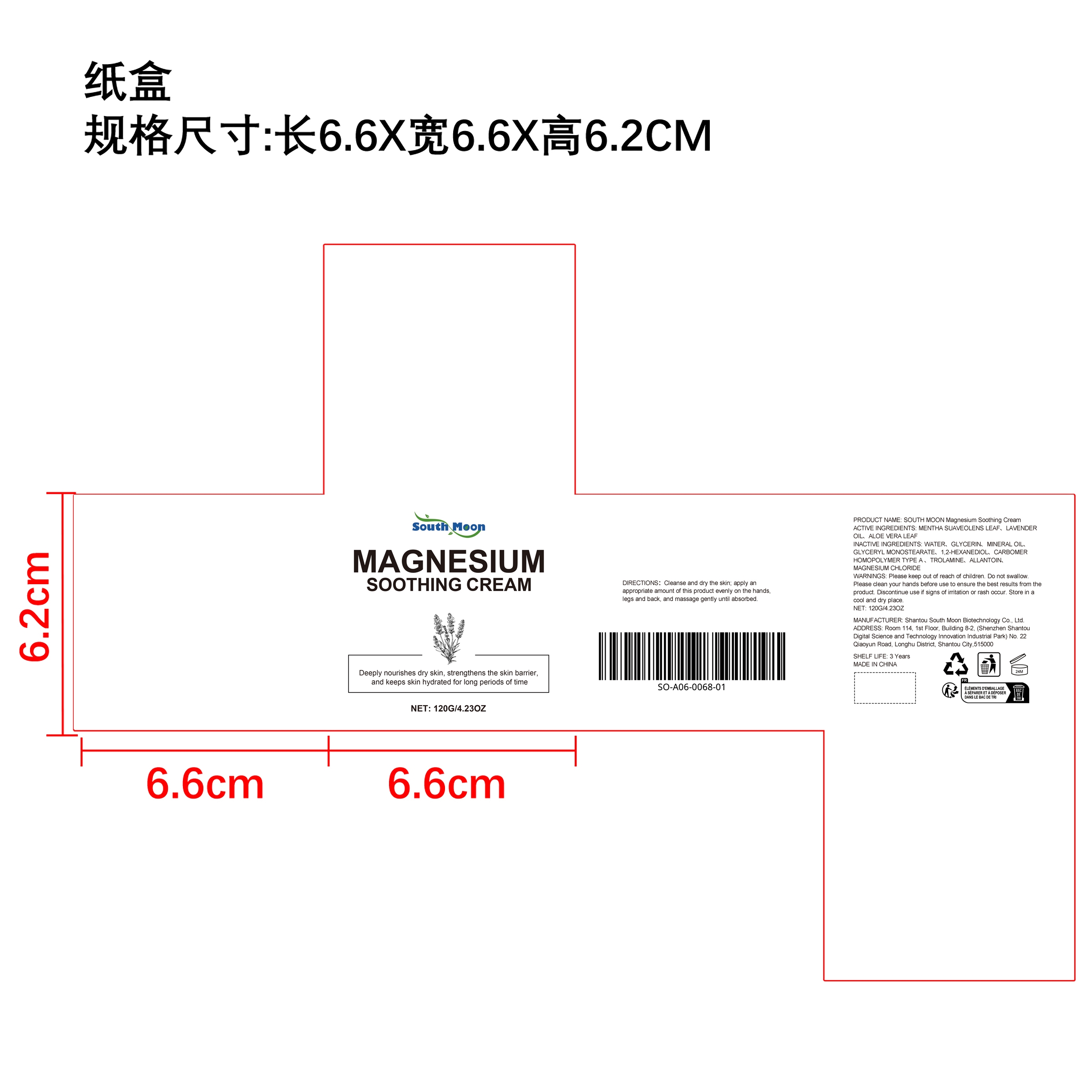 DRUG LABEL: SOUTH MOON Magnesium Soothing Cream
NDC: 84983-018 | Form: CREAM
Manufacturer: Shantou South Moon Biotechnology Co., Ltd.
Category: otc | Type: HUMAN OTC DRUG LABEL
Date: 20251127

ACTIVE INGREDIENTS: LAVENDER OIL 0.12 mg/120 mg; MENTHA SUAVEOLENS LEAF 0.12 mg/120 mg; ALOE VERA LEAF 0.12 mg/120 mg
INACTIVE INGREDIENTS: MINERAL OIL 3.6 mg/120 mg; GLYCERIN 9.6 mg/120 mg; MAGNESIUM CHLORIDE 0.12 mg/120 mg; GLYCERYL MONOSTEARATE 2.4 mg/120 mg; TROLAMINE 0.24 mg/120 mg; CARBOMER HOMOPOLYMER TYPE A 0.24 mg/120 mg; 1,2-HEXANEDIOL 0.6 mg/120 mg; ALLANTOIN 0.12 mg/120 mg; WATER 102.72 mg/120 mg

ACTIVE INGREDIENT

MENTHA SUAVEOLENS LEAF、LAVENDER OIL、ALOE VERA LEAF

PURPOSE

1. Deeply moisturize the skin, replenish the skin's moisture barrier and prevent moisture loss.

2. Enhance the skin's water-locking ability, repair and nourish the skin at night, so that the skin can be fully hydrated and moisturized during the rest period.

3. Enhance the hydration of the skin, keep the skin moist and plump for a long time, improve dryness and roughness, and make the skin look healthier and shiny.

WHEN USING

Relieve nerve pain and promote blood circulation; deeply nourish the skin and improve dry skin; enhance skin vitality and provide a relaxing experience.

WARNINGS

Please keep out of reach of children. Do not swallow.Please clean your hands before use to ensure the best results from the product. Discontinue use if signs of irritation or rash occur. Store in a cool and dry place.

DO NOT USE

Discontinue use if signs of irritation or rash occur.

STOP USE

Discontinue use if signs of irritation or rash occur.

KEEP OUT OF REACH OF CHILDREN

Please keep out of reach of children. Do not swallow.

STORAGE AND HANDLING

Store in a cool and dry place.

INACTIVE INGREDIENT

WATER、GLYCERIN、MINERAL OIL、GLYCERYL MONOSTEARATE、1,2-HEXANEDIOL、CARBOMER HOMOPOLYMER TYPE A 、TROLAMINE、ALLANTOIN、MAGNESIUM CHLORIDE

INDICATIONS AND USAGE

Relieve nerve pain and promote blood circulation; deeply nourish the skin and improve dry skin; enhance skin vitality and provide a relaxing experience.

DOSAGE AND ADMINISTRATION

Relieve nerve pain and promote blood circulation; deeply nourish the skin and improve dry skin; enhance skin vitality and provide a relaxing experience.